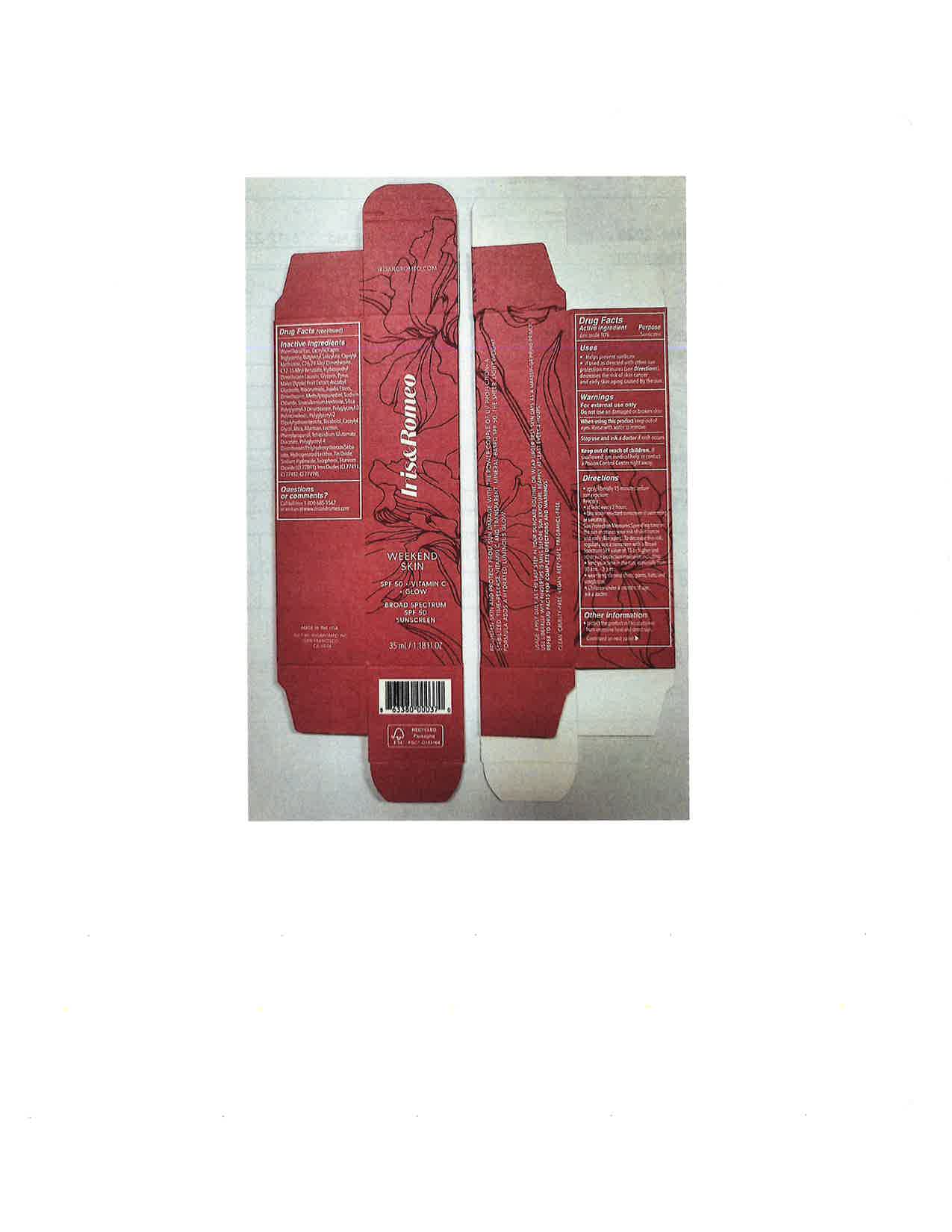 DRUG LABEL: Iris and Romeo Weekend Skin
NDC: 83247-1321 | Form: LOTION
Manufacturer: Iris and Romeo
Category: otc | Type: HUMAN OTC DRUG LABEL
Date: 20251031

ACTIVE INGREDIENTS: ZINC OXIDE 132 mg/1 mL
INACTIVE INGREDIENTS: ASCORBYL GLUCOSIDE; HYDROLYZED JOJOBA ESTERS (ACID FORM); DIMETHICONE; METHYLPROPANEDIOL; STEARALKONIUM HECTORITE; SILICON DIOXIDE; POLYGLYCERYL-3 DIISOSTEARATE; CAPRYLYL GLYCOL; ALLANTOIN; LECITHIN, SOYBEAN; PHENYLPROPANOL; POLYGLYCERYL-4 DIISOSTEARATE/POLYHYDROXYSTEARATE/SEBACATE; FERRIC OXIDE RED; FERRIC OXIDE YELLOW; FERROSOFERRIC OXIDE; ALKYL (C12-15) BENZOATE; BUTYLOCTYL SALICYLATE; .ALPHA.-BISABOLOL, (+)-; SODIUM HYDROXIDE; WATER; NIACINAMIDE; TETRASODIUM GLUTAMATE DIACETATE; SODIUM CHLORIDE; POLYGLYCERYL-2 DIPOLYHYDROXYSTEARATE; TITANIUM DIOXIDE; MICA; TOCOPHEROL; STANNIC OXIDE; GLYCERIN

Iris and Romeo Weekend Skin